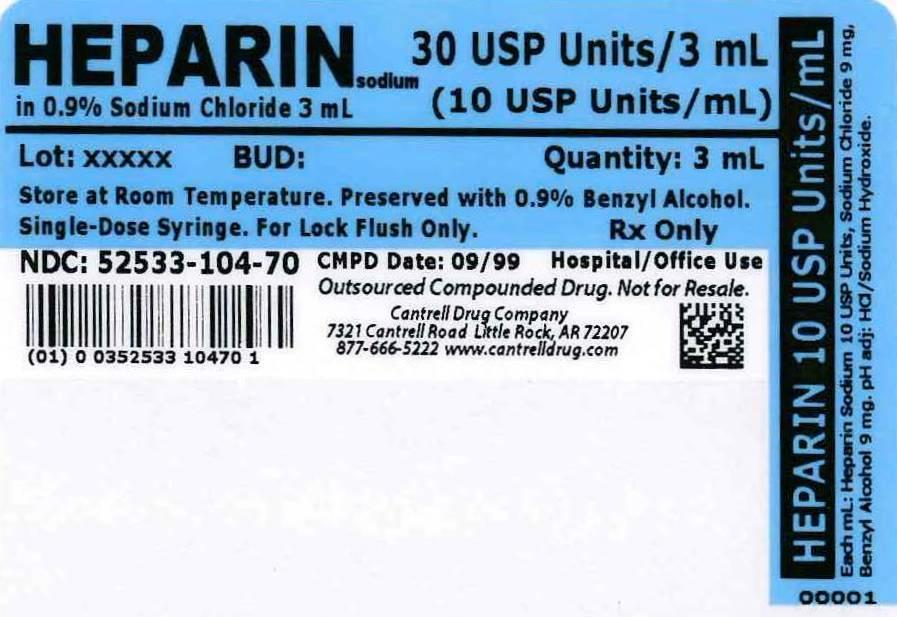 DRUG LABEL: Heparin Sodium
NDC: 52533-104 | Form: INJECTION, SOLUTION
Manufacturer: Cantrell Drug Company
Category: prescription | Type: HUMAN PRESCRIPTION DRUG LABEL
Date: 20140528

ACTIVE INGREDIENTS: HEPARIN SODIUM 10 [USP'U]/1 mL
INACTIVE INGREDIENTS: Sodium Chloride 9 mg/1 mL; BENZYL ALCOHOL 9 mg/1 mL; Water

Heparin Sodium 10 USP Units/mL in 0.9% Sodium Chloride 3 mL Syringe